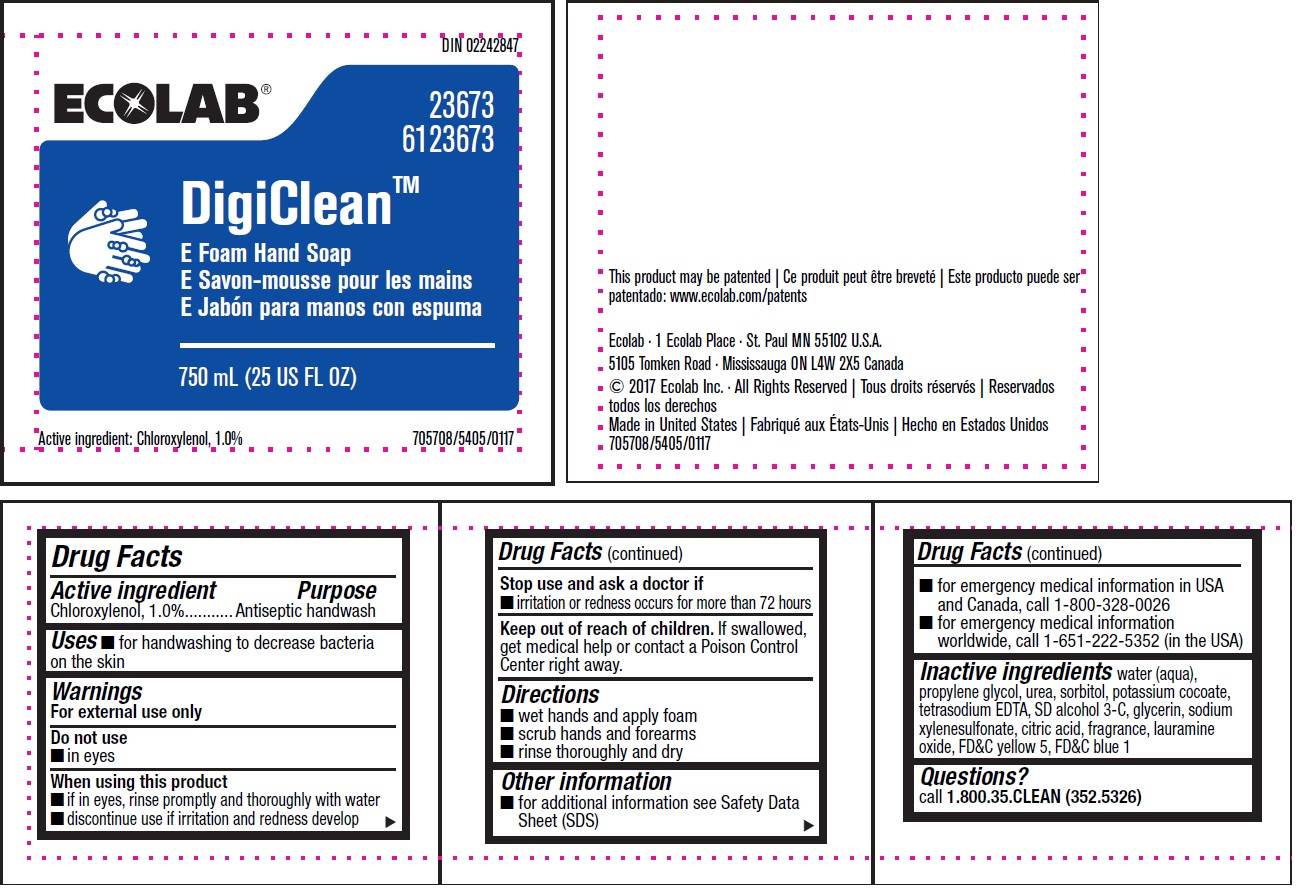 DRUG LABEL: DigiClean E
NDC: 47593-308 | Form: SOLUTION
Manufacturer: Ecolab Inc.
Category: otc | Type: HUMAN OTC DRUG LABEL
Date: 20240315

ACTIVE INGREDIENTS: CHLOROXYLENOL 1.0 mg/100 mL
INACTIVE INGREDIENTS: WATER; PROPYLENE GLYCOL; UREA; SORBITOL; POTASSIUM COCOATE; EDETATE SODIUM; ALCOHOL; GLYCERIN; SODIUM XYLENESULFONATE; ANHYDROUS CITRIC ACID; LAURAMINE OXIDE; FD&C YELLOW NO. 5; FD&C BLUE NO. 1

Drug Facts

Active Ingredient

Chloroxylenol, 1.0%

Purpose

Antiseptic handwash

Uses

- for handwashing to decrease bacteria on the skin

Warnings

For external use only

Do not use

- In eyes

When using this product

- if in eyes, rinse promptly and thoroughly with water
- discontinue use if irritation and redness develop

Stop use and ask a doctor if

- irritation or redness occurs for more than 72 hours

Keep out of reach of children. If swallowed, get medical help or contact a Poison Control Center right away.

Directions

- Wet hands and apply foam
- Scrub hands and forearms
- Rinse thoroughly and dry

Other information

- For additional information see Safety Data Sheet (SDS)
- For emergency medical information in USA and Canada, call 1-800-328-0026
- For emergency medical information worldwide, call 1-651-222-5352 (in the USA)

Inactive ingredients

Inactive ingredients water (aqua), propylene glycol, urea, sorbitol, potassium cocoate, tetrasodium EDTA, SD alcohol 3-C, glycerin, sodium xylenesulfonate, citric acid, fragrance, lauramine oxide, FD&C yellow 5, FD&C blue 1

Questions?

Call 1.800.35.CLEAN (352.5326)

Principal Display Panel

DIN 02242847

ECOLAB

23673

6123673

DigiClean™

E Foam Hand Soap

750 mL (25 US FL OZ)

Active Ingredient: Chloroxylenol, 1.0%

705708/5405/0117

This product may be patented

patentado: www.ecolab.com/patents

Ecolab · 1 Ecolab Place · St. Paul MN 55102 U.S.A.

5105 Tomken Road · Mississauga ON L4W 2X5 Canada

© 2017 Ecolab Inc. · All Rights Reserved

Made in United States

705708/5405/0117